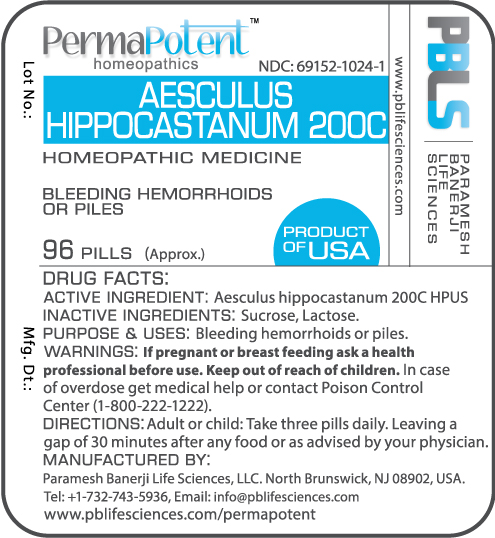 DRUG LABEL: Aesculus hippocastanum 200C
NDC: 69152-1024 | Form: PELLET
Manufacturer: Paramesh Banerji Life Sciences LLC
Category: homeopathic | Type: HUMAN OTC DRUG LABEL
Date: 20170216

ACTIVE INGREDIENTS: HORSE CHESTNUT 200 [hp_C]/1 1
INACTIVE INGREDIENTS: SUCROSE; LACTOSE

DRUG FACTS: Active Ingredient

Aesculus hippocastanum 200C HPUS

Inactive Ingredients

Sucrose, Lactose

Purpose

Bleeding hemorrhoids or piles

Uses

Bleeding hemorrhoids or piles

Warnings

If pregnant or breast feeding ask a health professional before use.

Keep out of reach of children. In case of overdose, get medical help or contact a Poison Control Center (1-800-222-1222) right away.

Direction

Adult or child: Take three pills daily. Leaving a gap of 30 minutes after any food or as advised by your physician.

Manufactured by

Paramesh Banerji Life Sciences, LLC.

North Brunswick, NJ 08902, USA.

Tel: +1-732-743-5936

Email: info@pblifesciences.com

Principal Display Panel

NDC: 69152-1024-1

Aesculus hippocastanum 200C

Homeopathic Medicine

Bleeding hemorrhoids or piles

96 Pills (approx.)

Product of USA